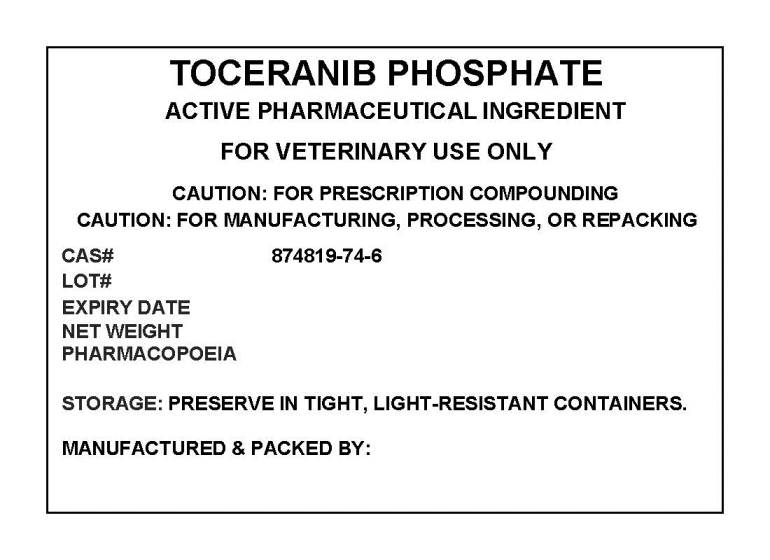 DRUG LABEL: TOCERANIB PHOSPHATE
NDC: 72969-072 | Form: POWDER
Manufacturer: PROFESSIONAL GROUP OF PHARMACISTS NEW YORK LLC
Category: other | Type: BULK INGREDIENT
Date: 20210311

ACTIVE INGREDIENTS: TOCERANIB PHOSPHATE 1 g/1 g

TOCERANIB PHOSPHATE

PACKAGE LABEL

toceraniblabel.jpg